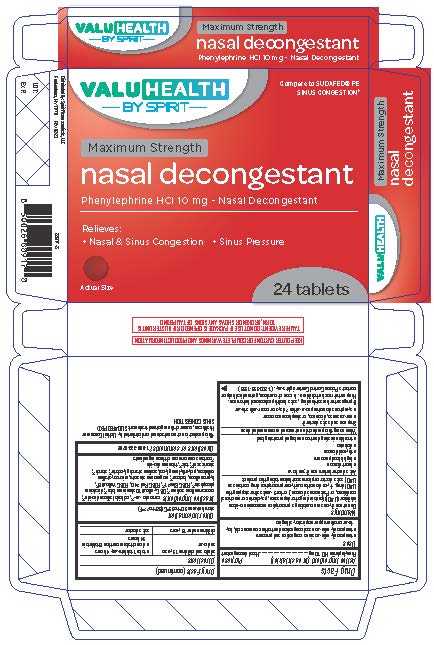 DRUG LABEL: Nasal Decongestant
NDC: 68210-4142 | Form: TABLET
Manufacturer: Spirit Pharmaceuticals LLC
Category: otc | Type: HUMAN OTC DRUG LABEL
Date: 20241213

ACTIVE INGREDIENTS: PHENYLEPHRINE HYDROCHLORIDE 10 mg/1 1
INACTIVE INGREDIENTS: MICROCRYSTALLINE CELLULOSE; POLYETHYLENE GLYCOL 400; SODIUM STARCH GLYCOLATE TYPE A CORN; STARCH, CORN; STEARIC ACID; TALC; TITANIUM DIOXIDE; CARNAUBA WAX; SILICON DIOXIDE; CROSCARMELLOSE SODIUM; D&C YELLOW NO. 10 ALUMINUM LAKE; ANHYDROUS DIBASIC CALCIUM PHOSPHATE; FD&C BLUE NO. 1; FD&C RED NO. 40; FD&C YELLOW NO. 6; HYPROMELLOSE, UNSPECIFIED; LACTOSE, UNSPECIFIED FORM; MAGNESIUM STEARATE

Nasal Decongestant Tablets

Drug Facts

Active ingredient (in each tablet)

Phenylephrine HCl 10 mg

Purpose

Nasal decongestant

Uses

■ temporarily relieves sinus congestion and pressure
■ temporarily relieves nasal congestion due to the common cold, hay
fever or other upper respiratory allergies

Warnings

Do not use if you are now taking a prescription monoamine oxidase
inhibitor (MAOI) (certain drugs for depression, psychiatric or emotional
conditions, or Parkinson's disease), or for 2 weeks after stopping the
MAOI drug. If you do not know if your prescription drug contains an
MAOI, ask a doctor or pharmacist before taking this product.

Ask a doctor before use if you have

■ heart disease
■ high blood pressure
■ thyroid disease
■ diabetes
■ trouble urinating due to an enlarged prostate gland

When using this product do not exceed recommended dose

Stop use and ask a doctor if

■ nervousness, dizziness, or sleeplessness occur
■ symptoms do not improve within 7 days or occur with a fever

PREGNANCY OR BREAST FEEDING

If pregnant or breast-feeding, ask a health professional before use.

Keep out of reach of children. In case of overdose, get medical help or
contact a Poison Control Center right away. (1-800-222-1222)

Directions

adults and children 12 years and over | ■ take 1 tablet every 4 hours ■ do not take more than 6 tablets in 24 hours
children under 12 years | ask a doctor

Other information

store between 20° to 25°C (68° to 77°F)

Inactive ingredients

carnauba wax*, colloidal silicon dioxide*, croscarmellose sodium*, D&C yellow#10 aluminum lake*, dicalcium phosphate*, FD&C Blue#1*, FD&C Red #40 , FD&C Yellow#6*, hypromellose, lactose*, magnesium stearate, microcrytalline cellulose, polyethylene glycol, sodium starch glycolate*, starch*, stearic acid*, talc*, titanium dioxide
*contains one or more of these ingredients

Questions or comments? 1-888-333-9792

PRINCIPAL DISPLAY PANEL

Maximum Strength
Nasal Decongestant
Phenylephrine HCl 10 mg - Nasal Decongestant

Relieves:
• Nasal & Sinus Congestion • Sinus Pressure

24 Tablets